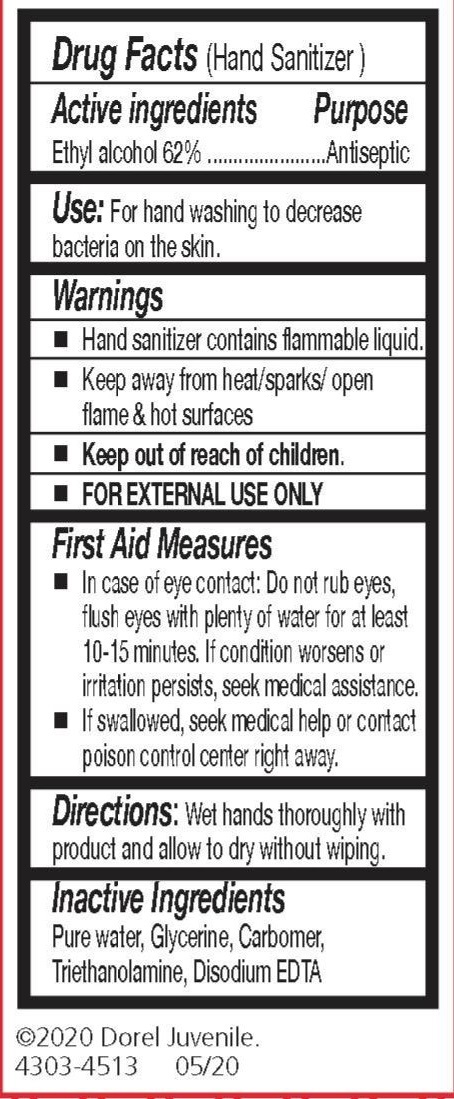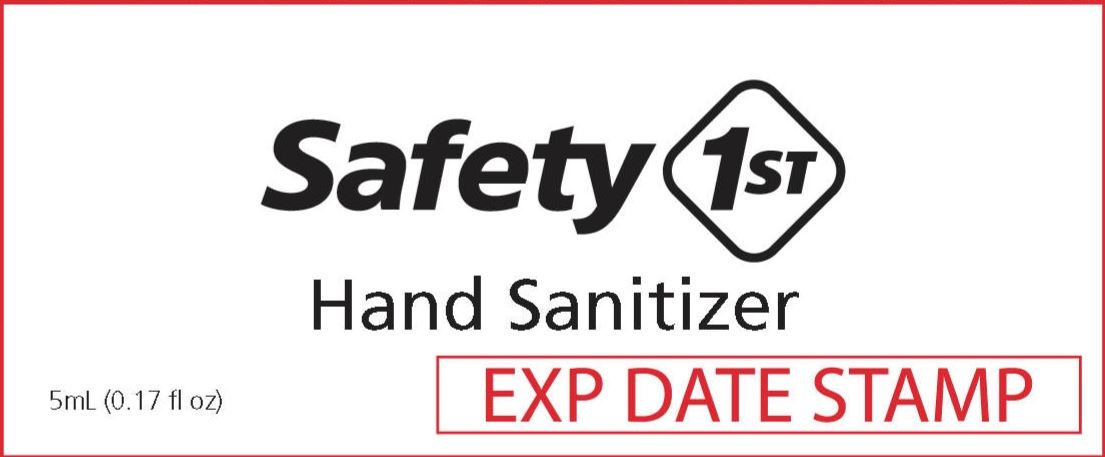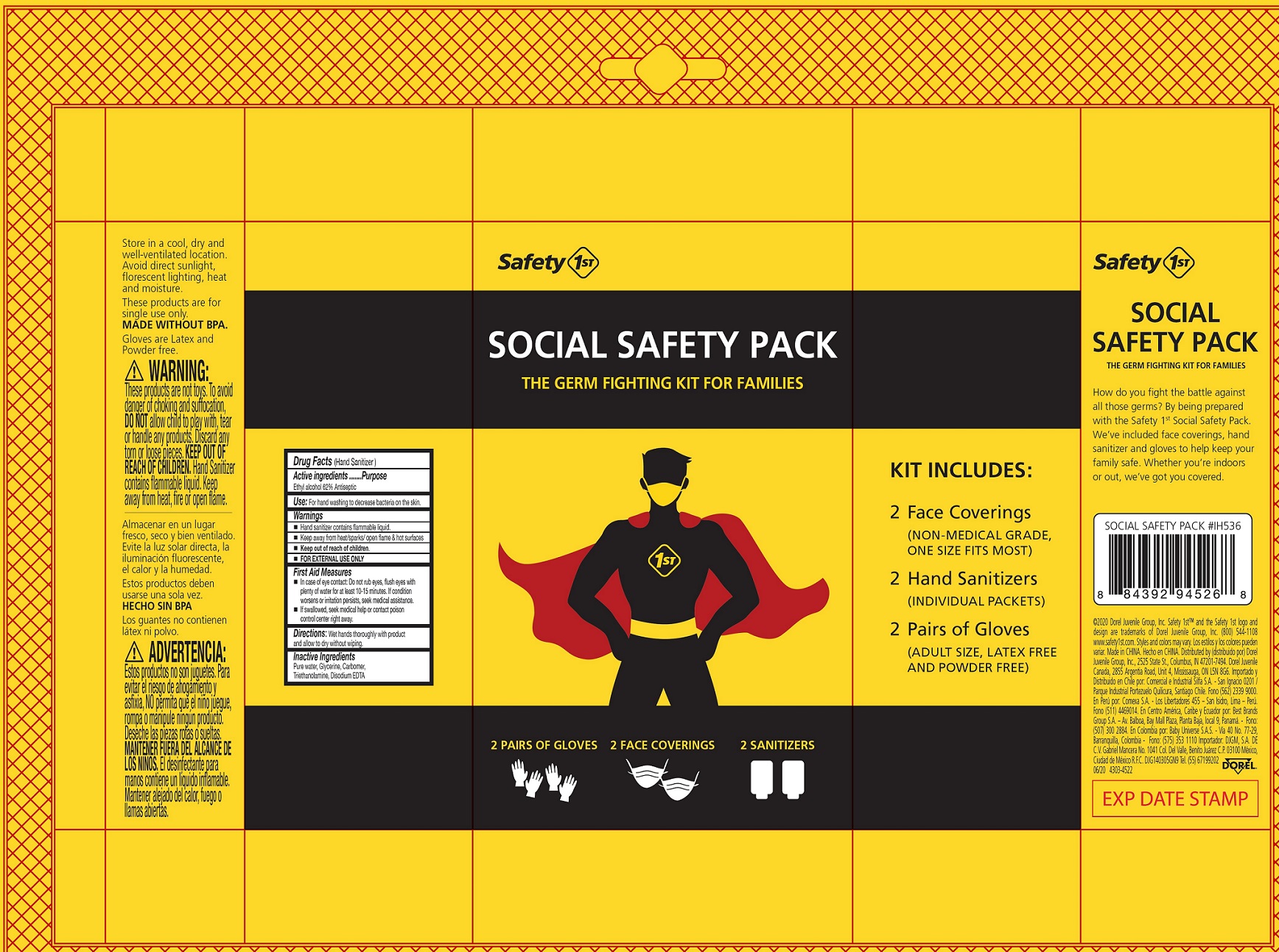 DRUG LABEL: Safety 1st Social Safety Pack
NDC: 50428-0031 | Form: KIT | Route: TOPICAL
Manufacturer: Dorel Juvenile Inc.
Category: otc | Type: HUMAN OTC DRUG LABEL
Date: 20231023

ACTIVE INGREDIENTS: ALCOHOL 0.62 mL/1 mL
INACTIVE INGREDIENTS: WATER; GLYCERIN; CARBOMER HOMOPOLYMER, UNSPECIFIED TYPE; TROLAMINE; EDETATE DISODIUM ANHYDROUS

Safety 1st Social Safety Pack

Active ingredients

Ethyl alcohol 62%

Purpose

Antiseptic

Use:

For hand washing to decrease bacteria on the skin.

Warnings

- Hand sanitizer contains flammable liquid.
- Keep away from heat/sparks/ open flame & hot surfaces
- FOR EXTERNAL USE ONLY

First Aid Measures

- In case of eye contact: Do not rub eyes, flush eyes with plenty of water for at least 10-15 minutes. If condition worsens or irritation persists, seek medical assistance.
- If swallowed, seek medical help or contact poison control center right away.

Directions:

Wet hands thoroughly with product and allow to dry without wiping.

Inactive Ingredients

Pure water, Glycerine, Carbomer, Triethanolamine, Disodium EDTA